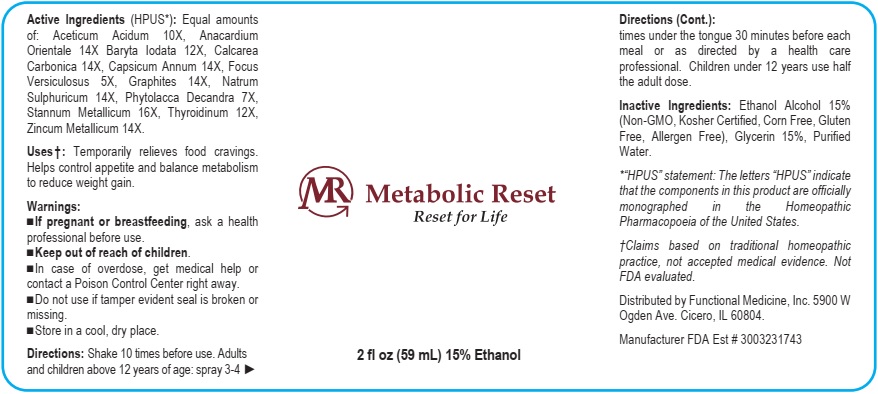 DRUG LABEL: Metabolic Reset
NDC: 72638-001 | Form: LIQUID
Manufacturer: Hanoun, Andrew Functional Medicine Inc.
Category: homeopathic | Type: HUMAN OTC DRUG LABEL
Date: 20210121

ACTIVE INGREDIENTS: ACETIC ACID 10 [hp_X]/59 mL; SEMECARPUS ANACARDIUM JUICE 14 [hp_X]/59 mL; BARIUM IODIDE 12 [hp_X]/59 mL; OYSTER SHELL CALCIUM CARBONATE, CRUDE 14 [hp_X]/59 mL; CAPSICUM 14 [hp_X]/59 mL; FUCUS VESICULOSUS 5 [hp_X]/59 mL; GRAPHITE 14 [hp_X]/59 mL; SODIUM SULFIDE NONAHYDRATE 14 [hp_X]/59 mL; PHYTOLACCA AMERICANA ROOT 7 [hp_X]/59 mL; TIN 16 [hp_X]/59 mL; THYROID, UNSPECIFIED 12 [hp_X]/59 mL; ZINC 14 [hp_X]/59 mL
INACTIVE INGREDIENTS: ALCOHOL; GLYCERIN; WATER

Metabolic Reset

Active Ingredients (HPUS*): Equal amounts

of: Aceticum Acidum 10X, Anacardium

Orientale 14X Baryta Iodata 12X, Calcarea

Carbonica 14X, Capsicum Acidum 14X, Focus

Versiculosus 5X, Graphites 14X, Natrum

Sulphuricum 14X, Phytolacca Decandra 7X,

Stannum Metallicum 16X, Thyroidinum 12X

Zincum Metallicum 14X

*" HPUS" statement: The letters "HPUS" indicate

that the components in this product are officially

monographed in the Homeopathic

Pharmacopoeia of the Unites States.

† Claims based on traditional homeopathic

practice, not accepted medical evidence. Not

FDA evaluated.

INDICATIONS AND USAGE

Uses†: Temporarily relieves food cravings.

Helps control appetite and balance metabolism

to reduce weight gain.

Warnings:

•If pregnant or breastfeeding, ask a health

professional before use.

•Keep out of reach of children.

•In case of overdose, get medical help or

contact a Poison Control Center right away.

•Do not use if tamper evident seal is broken or

missing.

•Store in a cool, dry place.

•Keep out of reach of children.

DOSAGE AND ADMINISTRATION

Directions: Shake 10 times before use. Adults

and children above 12 years of age: spray 3-4

times under the tongue 30 minutes before each

meal or as directed by a health care

professional. Children under 12 years use half

the adult dose.

Inactive Ingredients: Ethanol Alcohol 15%

(Non-GMA, Kosher Certified, Corn Free, Gluten

Free, Allergen Free), Glycerin 15%, Purified

Water.

QUESTIONS

Distributed by Functional Medicine, Inc. 5900 W

Odgen Ave. Cicero, IL 60804

Manufacturer FDA Est # 3003231743

PACKAGE LABEL

Metabolic Reset

Reset for Life

2 fl oz (59 mL) 15% Ethanol

PURPOSE

Temporarily relieves food cravings.

Helps control appetite and balance metabolism

to reduce weight gain.